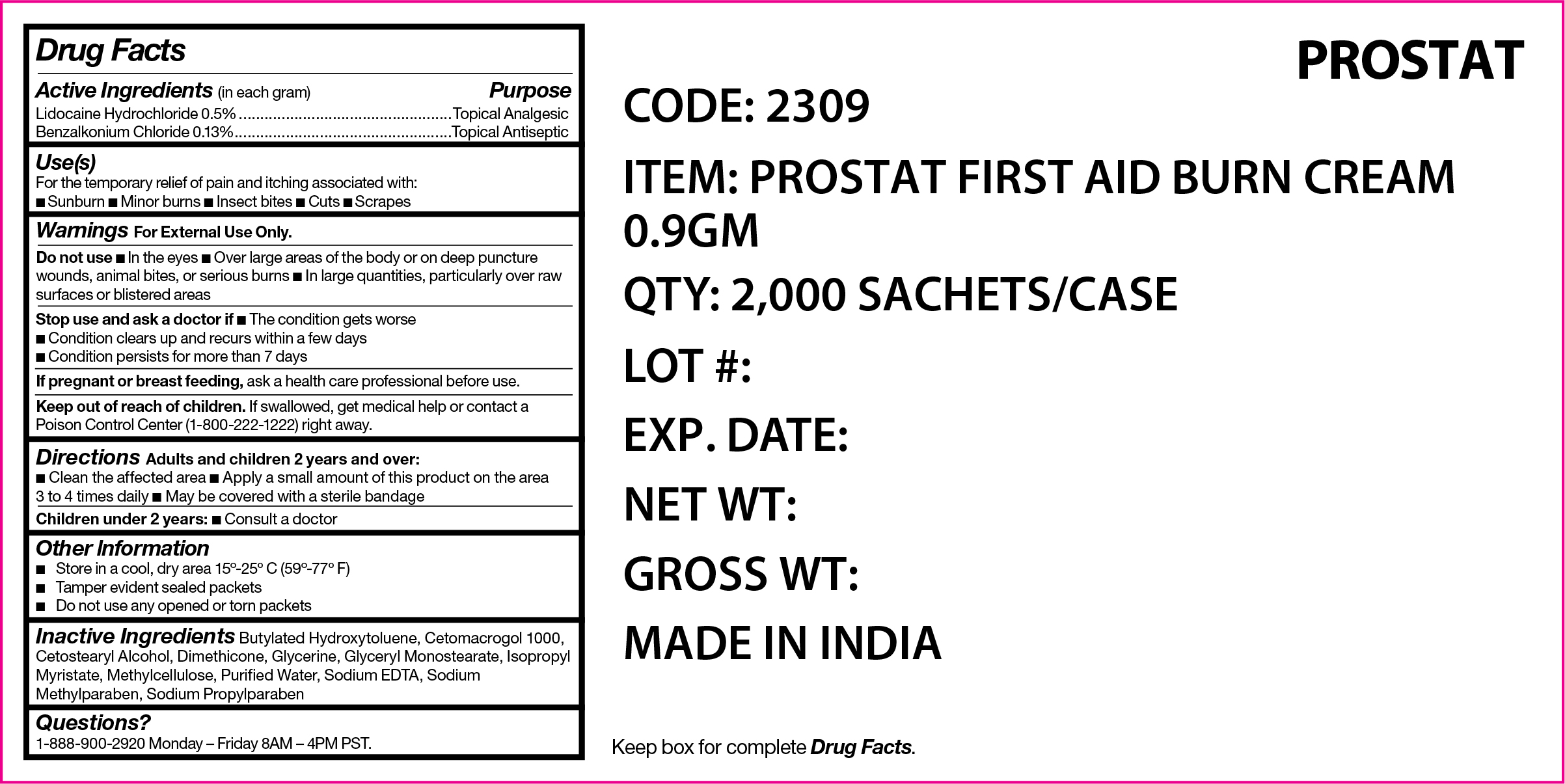 DRUG LABEL: First Aid Burn Cream
NDC: 58228-2309 | Form: CREAM
Manufacturer: ProStat First Aid LLC
Category: otc | Type: HUMAN OTC DRUG LABEL
Date: 20251215

ACTIVE INGREDIENTS: LIDOCAINE HYDROCHLORIDE 50 mg/10000 mg; BENZALKONIUM CHLORIDE 13 mg/10000 mg
INACTIVE INGREDIENTS: WATER; EDETATE SODIUM; BUTYLATED HYDROXYTOLUENE; GLYCERYL MONOSTEARATE; METHYLCELLULOSE (4000 MPA.S); PROPYLPARABEN SODIUM; ISOPROPYL MYRISTATE; METHYLPARABEN SODIUM; CETETH-20; DIMETHICONE 350; GLYCERIN; CETOSTEARYL ALCOHOL

PS-2309 First Aid Burn Cream

Active Ingredient

Lidocaine HCI 0.5%

Purpose

Topical Analgesic

Active Ingredient

Benzalkonium Chloride 0.13%

Purpose

Topical Antiseptic

Use(s)

For the temporary relief of pain and itching associated with:

• Sunburn • Minor burns • Insect bites • Cuts • Scrapes

Warnings

For External Use Only.

Do not use

• In the eyes • Over large areas of the body or on deep puncture wounds, animal bites, or serious burns • In large quantities, particularly over raw surfaces or blistered areas

Stop use and ask a doctor if

• The condition gets worse • Condition clears up and recurs within a few days • Condition persists for more than 7 days

If pregnant or breast feeding

Ask a health care professional before use.

Keep out of reach of children

If swallowed, get medical help or contact a Poison Control Center (1-800-222-1222) right away.

Directions

Adults and children 2 years and over:

• Clean the affected area • Apply a small amount of this product on the area 3 to 4 times daily • May be covered with a sterile bandage

Children under 2 years:

• Consult a doctor

Other Information

• Store in a cool, dry area 15º-25ºC (59º-77ºF)

• Tamper evident sealed packets

• Do not use any opened or torn packets

Inactive Ingredients

Butylated Hydroxytoluene, Cetomacrogol 1000, Cetostearyl Alcohol, Dimethicone, Gylcerine, Glyceryl Monostearate, Isopropyl Myristate, Methylcellulose, Purified Water, Sodium EDTA, Sodium Methylparaben, Sodium Propylparaben

Questions?

1-888-900-2920 Monday - Friday 8AM - 4PM PST.

Label

PS-2309 First Aid Burn Cream